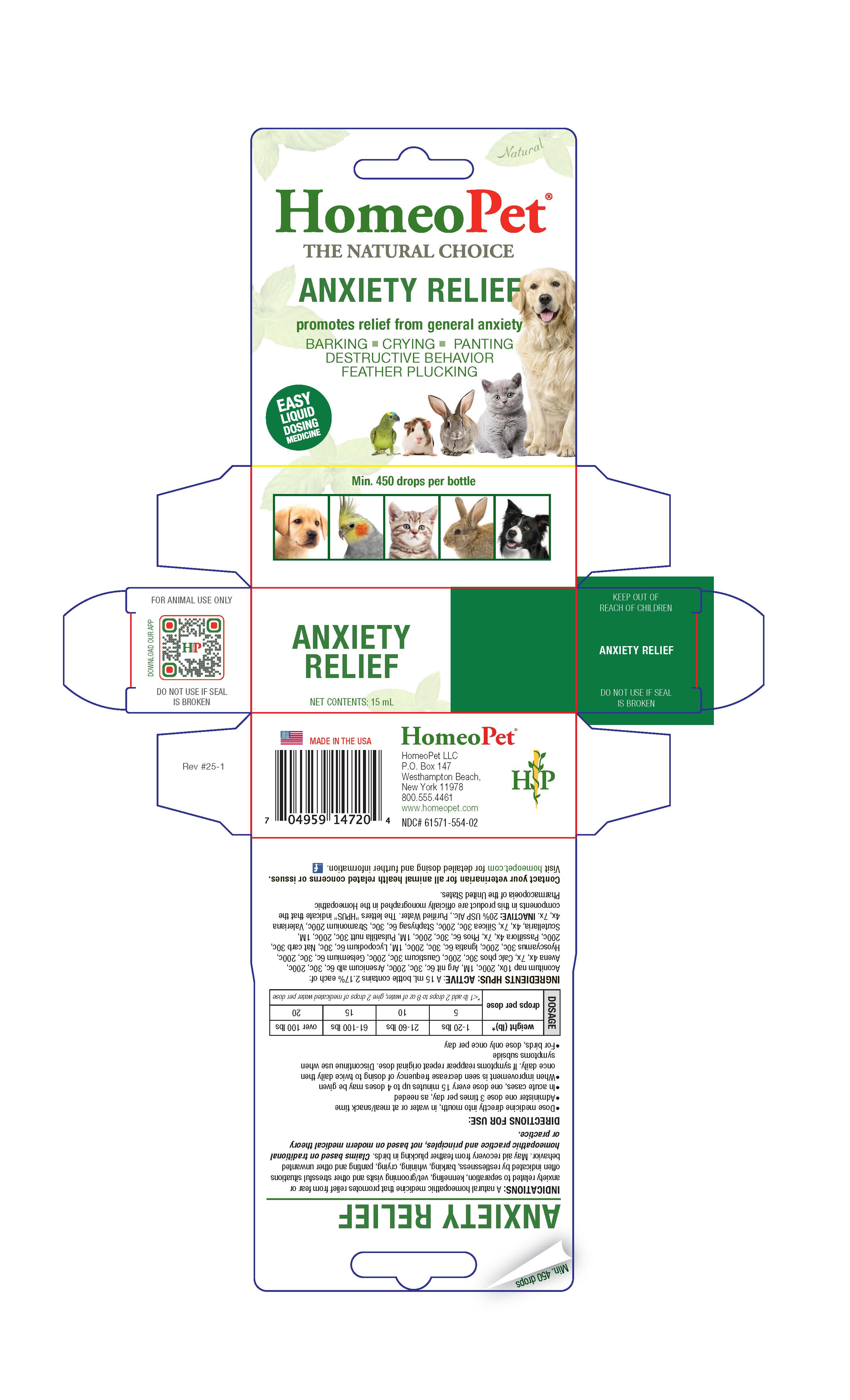 DRUG LABEL: Anxiety Relief
NDC: 61571-554 | Form: LIQUID
Manufacturer: HomeoPet, LLC
Category: homeopathic | Type: OTC ANIMAL DRUG LABEL
Date: 20251216

ACTIVE INGREDIENTS: ACONITUM NAPELLUS 10 [hp_X]/15 mL; SILVER NITRATE 6 [hp_C]/15 mL; ARSENIC TRIOXIDE 6 [hp_C]/15 mL; AVENA SATIVA FLOWERING TOP 4 [hp_X]/15 mL; TRIBASIC CALCIUM PHOSPHATE 30 [hp_C]/15 mL; CAUSTICUM 30 [hp_C]/15 mL; GELSEMIUM SEMPERVIRENS ROOT 6 [hp_C]/15 mL; HYOSCYAMUS NIGER 6 [hp_C]/15 mL; STRYCHNOS IGNATII SEED 6 [hp_C]/15 mL; LYCOPODIUM CLAVATUM SPORE 6 [hp_C]/15 mL; SODIUM CARBONATE 30 [hp_C]/15 mL; PASSIFLORA INCARNATA TOP 4 [hp_X]/15 mL; PHOSPHORUS 6 [hp_C]/15 mL; PULSATILLA PATENS 30 [hp_C]/15 mL; SCUTELLARIA LATERIFLORA 4 [hp_X]/15 mL; SILICON DIOXIDE 30 [hp_C]/15 mL; DELPHINIUM STAPHISAGRIA SEED 6 [hp_C]/15 mL; DATURA STRAMONIUM 200 [hp_C]/15 mL; VALERIAN  4 [hp_X]/15 mL
INACTIVE INGREDIENTS: ALCOHOL; WATER

Anxiety Relief

Anxiety Relief

Promotes relief from general anxiety
Barking-Crying-Panting-Destructive Behavior-Feather Plucking

Direction for Use and Dosing Information

- Dose remedy directly into mouth, in water or at meal/snack time
- Administer one dose 3 times per day, as needed
- In acute cases, one dose every 15 minutes up to 4 doses may be given
- When improvement is seen decrease frequency of dosing to twice daily then once daily. If symptoms reappear repeat original dose. Discontinue use when symptoms subside
- For birds dose only once per day

weight (lb) | drops per dose
animals less than 1 lb | 2 in at least 8 oz of water
1-20 | 5
21-60 | 10
61-100 | 15
over 100 | 20

Indications

A natural homeopathic medicine that promotes relief from fear or anxiety related to separation, kenneling, vet/grooming visits and other stressful situations often indicated by restlessness, barking, whining, crying, panting and other unwanted behavior. May aid recovery from feather plucking in birds. Claims based on traditional homeopathic practice and principles, not based on modern medical theory or practice.

ASK DOCTOR

Contact your veterinarian for all animal health related concerns or issues.

Visit homeopet.com for detailed dosing and further information.

Ingredients HPUS

Aconitum nap 10x, 200c, 1M, Arg nit, Arsenicum Alb 6c, 30c, 200c, Avena, Passiflora, Scutellaria, Valeriana 4x, 7x, Cal phos,
Causticum, Hyoscyamus, Nat carb, Silicea 30c, 200c, Gelsemium 6c, 30c, 200c, Ignatia, Phos 6c, 30c, 200c, 1M, Lycopodium, Staphysag 6c, 30c, Pulsatilla nutt 30c, 200c, 1M, Stramonium 200c

Inactive Ingredients

USP Alcohol, Purified Water